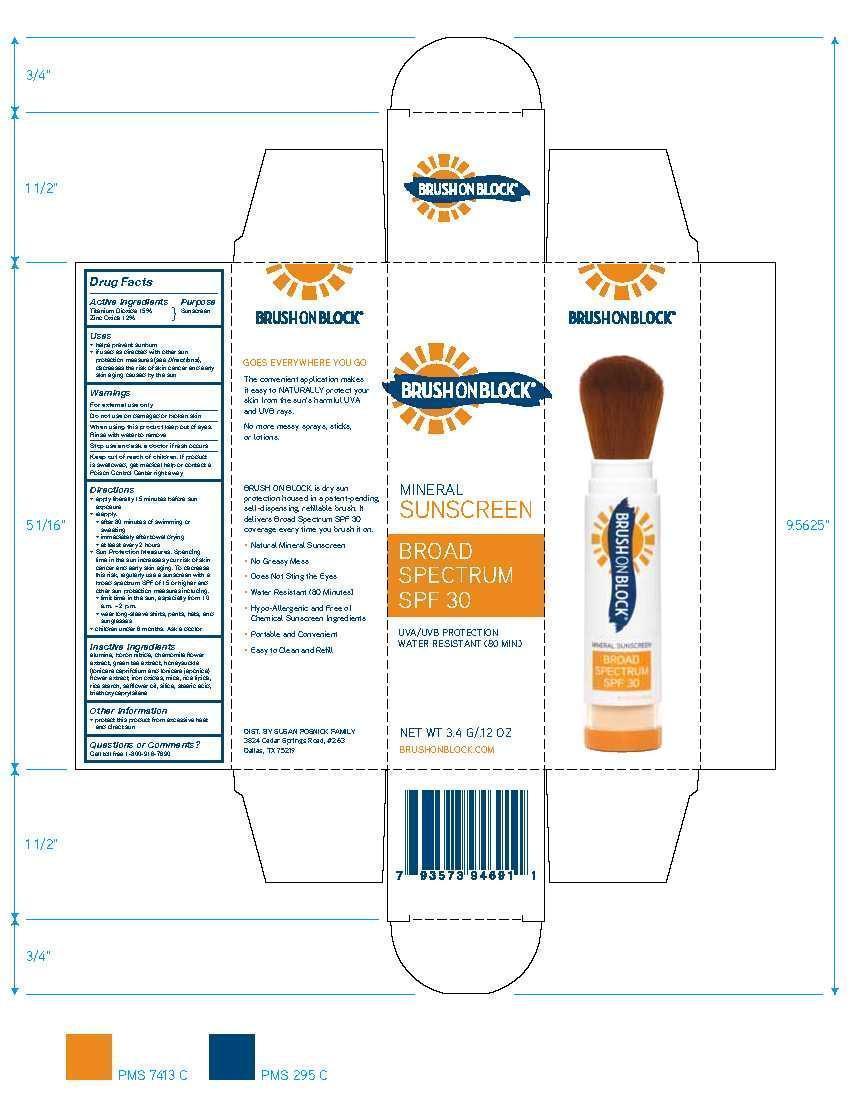 DRUG LABEL: Brush on Block Mineral Sunscreen Broad Spectrum SPF 30
NDC: 58274-006 | Form: CREAM
Manufacturer: SPF Ventures, LLC
Category: otc | Type: HUMAN OTC DRUG LABEL
Date: 20151015

ACTIVE INGREDIENTS: TITANIUM DIOXIDE 15 g/100 g; ZINC OXIDE 12 g/100 g
INACTIVE INGREDIENTS: ALUMINUM OXIDE; BORON NITRIDE; CHAMAEMELUM NOBILE FLOWER; GREEN TEA LEAF; LONICERA JAPONICA FLOWER; LONICERA CAPRIFOLIUM FLOWER; FERRIC OXIDE RED; MICA; STARCH, RICE; SAFFLOWER OIL; SILICON DIOXIDE; STEARIC ACID; TRIETHOXYCAPRYLYLSILANE; RICE BRAN

Brush on Block

Drug Facts

Active Ingredients

Titanium Dioxide 15%

Zinc Oxide 12%

Purpose

Sunscreen

Uses

- helps prevent sunburn
- if used as directed with other sun protection measures (see Directions), decreases risk of skin cancer and early skin aging caused by the sun

Directions

- apply liberally 15 minutes before sun exposure
- reapply: after 80 minutes of swimming or sweating, immediately after towel drying, and at least every 2 hours
- Sun Protection Measures: Spending time in the sun increases your risk of skin cancer and early skin aging. To decrease this risk, regularly use sunscreen with a broad spectrum SPF of 15 or higher and other sun protection measures including: limit time in the sun, especially from 10 a.m. - 2 p.m. and wear long-sleeve shirts, pants, hats, and sunglasses
- children under 6 months: Ask a doctor

Warnings

For external use only

Do not use on damaged or broken skin

When using this product keep out of eyes. Rinse with water to remove.

Stop use and ask a doctor if rash occurs

Keep out of reach of children. If product is swallowed, get medical help or contact a Poison Control Center right away

Questions or Comments?

Call toll free 1-800-916-7690

Other Information

- protect this product from excessive heat and direct sun

PACKAGE LABEL

Brush on Block

Mineral Sunscreen

Broad Spectrum SPF 30

UVA/UVB Protection

Water Resistant (80 MIN)

NET WT 3.4 G/.12 OZ

BRUSHONBLOCK.COM